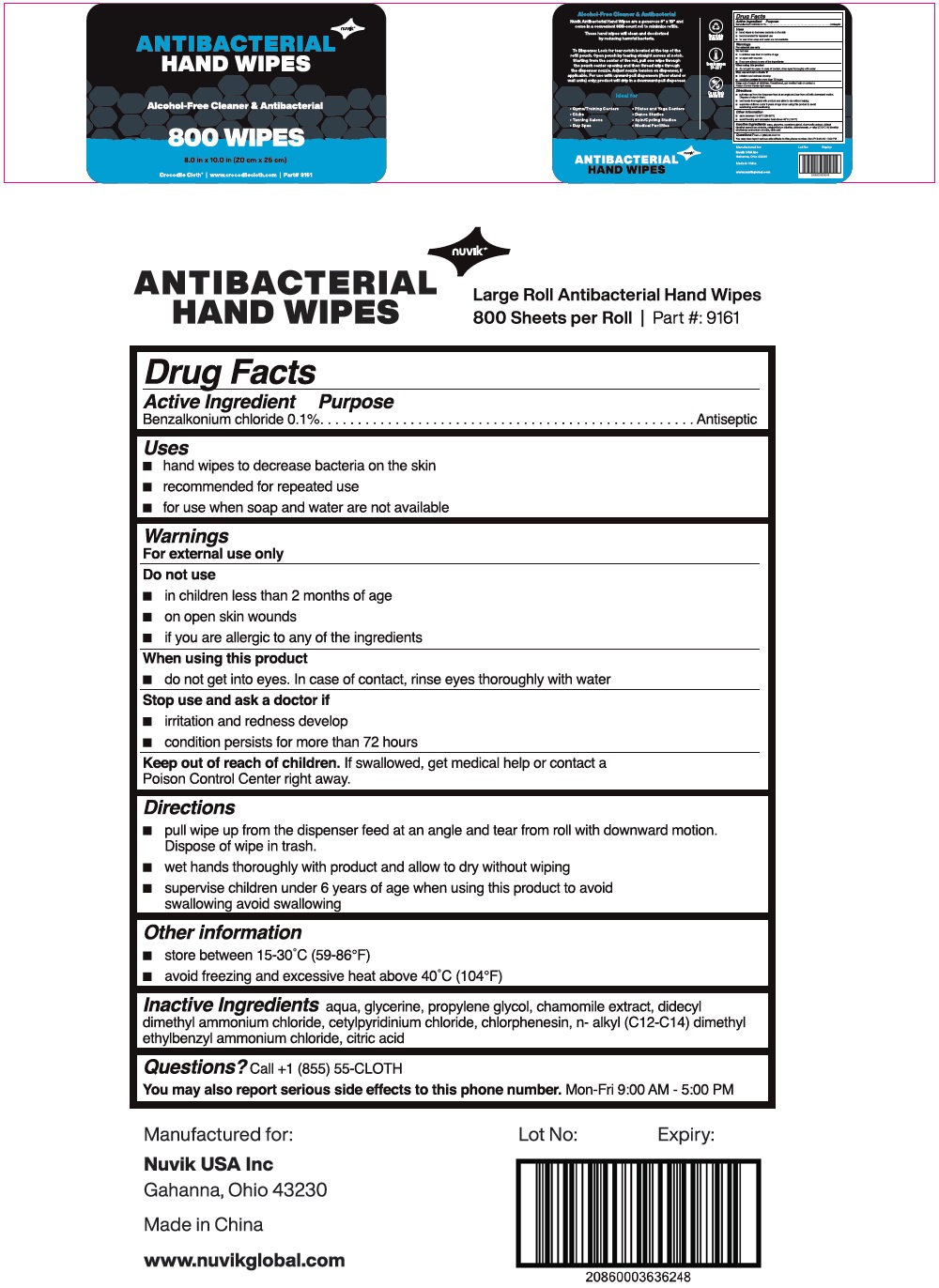 DRUG LABEL: Nuvik Large Roll in Bucket Antibacterial Hand Wipes
NDC: 74602-900 | Form: CLOTH
Manufacturer: Nuvik Usa, Inc.
Category: otc | Type: HUMAN OTC DRUG LABEL
Date: 20240618

ACTIVE INGREDIENTS: BENZALKONIUM CHLORIDE 0.1 g/100 mL
INACTIVE INGREDIENTS: WATER; GLYCERIN; PROPYLENE GLYCOL; CHAMOMILE; DIDECYLDIMONIUM CHLORIDE; CETYLPYRIDINIUM CHLORIDE; CHLORPHENESIN; N-ALKYL ETHYLBENZYL DIMETHYL AMMONIUM CHLORIDE (C12-C14); CITRIC ACID MONOHYDRATE

nuvik ANTIBACTERIAL HAND WIPES

Active Ingredient

Benzalkonium chloride 0.1%

Purpose

Antiseptic

Uses

■ hand wipes to decrease bacteria on the skin

■ recommended for repeated use

■ for use when soap and water are not available

Warnings

For external use only

Do not use

■ in children less than 2 months of age

■ on open skin wounds

■ if you are allergic to any of the ingredients

When using this product

■ do not get into eyes. In case of contact, rinse eyes thoroughly with water

Stop use and ask a doctor if

■ irritation and redness develop

■ condition persists for more than 72 hours

Keep out of reach of children. If swallowed, get medical help or contact a Poison Control Center right away.

Directions

■ pull wipe up from the dispenser feed at an angle and tear from roll with downward motion. Dispose of wipe in trash.

■ wet hands thoroughly with product and allow to dry without wiping

■ supervise children under 6 years of age when using this product to avoid swallowing

Other information

■ store between 15-30°C (59-86°F)

■ avoid freezing and excessive heat above 40°C (104°F)

Inactive Ingredients

aqua, glycerine, propylene glycol, chamomile extract, didecyl dimethyl ammonium chloride, cetylpyridinium chloride, chlorphenesin, n- alkyl (C12-C14) dimethyl ethylbenzyl ammonium chloride, citric acid

Questions?

Call +1 (855) 55-CLOTH

You may also report serious side effects to this phone number. Mon-Fri 9:00 AM - 5:00 PM

Alcohol-Free Cleaner & Antibacterial

Crocodile Cloth® | www.crocodilecloth.com | Part# 9161

Nuvik Antibacterial Hand Wipes are a generous 8" X 10" and come in a convenient 800-count roll to minimize refills. These hand wipes will clean and deodorized by reducing harmful bacteria.

To Dispense: Look for tear-notch located at the top of the refill pouch. Open pouch by tearing straight across at notch. Starting from the center of the roll, pull one wipe through the pouch center opening and then thread wipe through the dispenser nozzle. Adjust nozzle tension on dispenser, if applicable. For use with upward-pull dispensers (floor stand or wall units) only: product will drip in a downward-pull dispenser.

Ideal for

■ Gyms/Training Centers ■ Pilates and Yoga Centers

■ Clubs ■ Dance Studios

■ Tanning Salons ■ Spin/Cycling Studios

■ Day Spas ■ Medical Facilities

Recyclable packaging

Do not flush used wipes

Manufactured for:

Nuvik USA Inc

Gahanna, Ohio 43230

Made in China

www.nuvikglobal.com